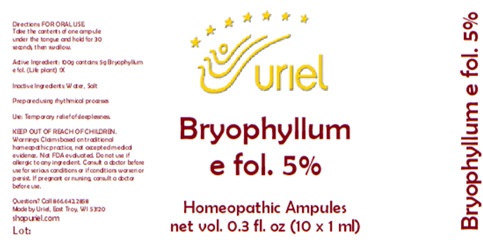 DRUG LABEL: Bryophyllum e fol. 5%
NDC: 48951-2099 | Form: LIQUID
Manufacturer: Uriel Pharmacy Inc.
Category: homeopathic | Type: HUMAN OTC DRUG LABEL
Date: 20250916

ACTIVE INGREDIENTS: KALANCHOE DAIGREMONTIANA LEAF 1 [hp_X]/1 mL
INACTIVE INGREDIENTS: WATER; SODIUM CHLORIDE

Bryophyllum e fol. 5

INDICATIONS AND USAGE

Directions: FOR ORAL USE.

DOSAGE AND ADMINISTRATION

Take the contents of one ampule under the tongue and hold for 30 seconds, then swallow.

Active Ingredient: 100g contains:
5g Bryophyllum e fol. (Life plant) 1X

Inactive Ingredients: Water, Salt

Prepared using rhythmical processes.

PURPOSE

Use: Temporary relief of sleeplessness.

KEEP OUT OF REACH OF CHILDREN.

WARNINGS

Warnings: Claims based on traditional homeopathic practice, not accepted medical evidence. Not FDA evaluated. Do not use if allergic to any ingredient. Consult a doctor before use for serious conditions or if conditions worsen or persist. If pregnant or nursing, consult a doctor before use.

Questions? Call 866.642.2858
Made by Uriel, East Troy, WI 53120
shopuriel.com

Lot: